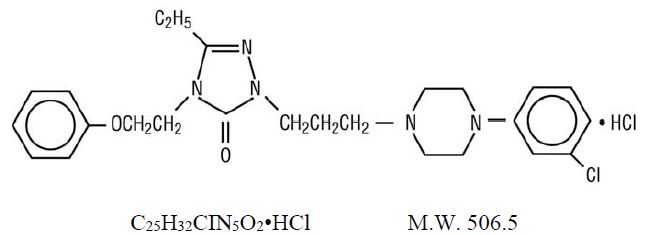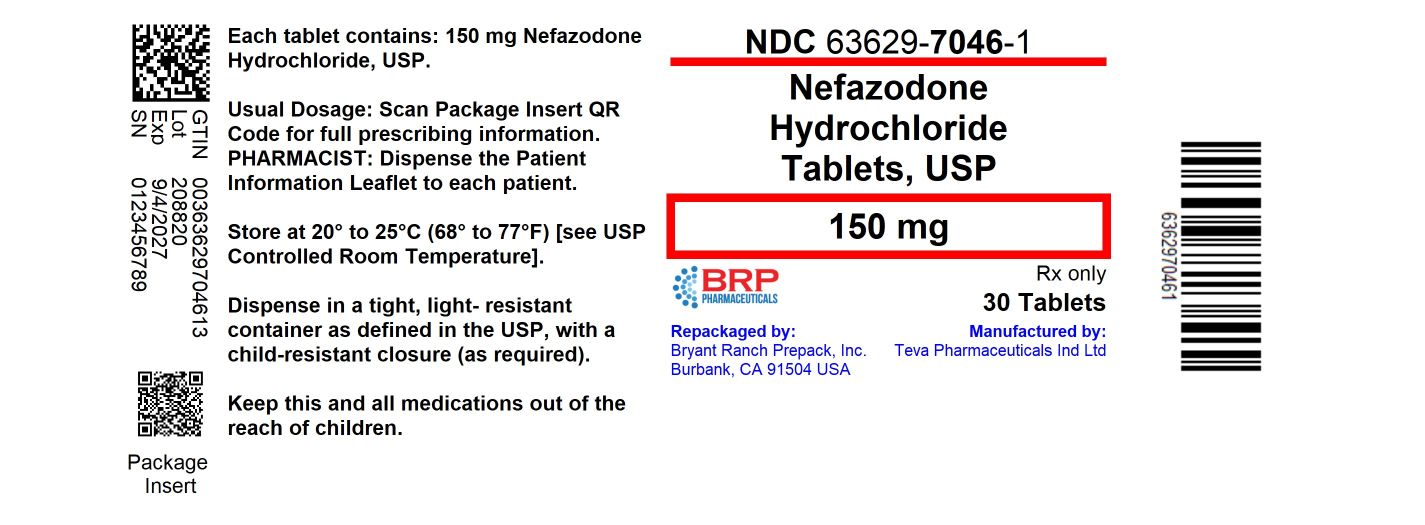 DRUG LABEL: Nefazodone Hydrochloride
NDC: 63629-7046 | Form: TABLET
Manufacturer: Bryant Ranch Prepack
Category: prescription | Type: HUMAN PRESCRIPTION DRUG LABEL
Date: 20250904

ACTIVE INGREDIENTS: NEFAZODONE HYDROCHLORIDE 150 mg/1 1
INACTIVE INGREDIENTS: SILICON DIOXIDE; MAGNESIUM STEARATE; MICROCRYSTALLINE CELLULOSE; SODIUM STARCH GLYCOLATE TYPE A POTATO; POVIDONE K30; FERRIC OXIDE RED; FERRIC OXIDE YELLOW

Nefazodone Hydrochloride Tablets, USP
Rx only
(Patient Information Included)

BOXED WARNING

Suicidality and Antidepressant Drugs

Antidepressants increased the risk compared to placebo of suicidal thinking and behavior (suicidality) in children, adolescents, and young adults in short-term studies of major depressive disorder (MDD) and other psychiatric disorders. Anyone considering the use of nefazodone hydrochloride tablets or any other antidepressant in a child, adolescent, or young adult must balance this risk with the clinical need. Short-term studies did not show an increase in the risk of suicidality with antidepressants compared to placebo in adults beyond age 24; there was a reduction in risk with antidepressants compared to placebo in adults aged 65 and older. Depression and certain other psychiatric disorders are themselves associated with increases in the risk of suicide. Patients of all ages who are started on antidepressant therapy should be monitored appropriately and observed closely for clinical worsening, suicidality, or unusual changes in behavior. Families and caregivers should be advised of the need for close observation and communication with the prescriber. Nefazodone hydrochloride tablets are not approved for use in pediatric patients (see WARNINGS, Clinical Worsening and Suicide Risk; PRECAUTIONS, Information for Patients; and PRECAUTIONS, Pediatric Use).

Before prescribing nefazodone hydrochloride tablets, the physician should be thoroughly familiar with the details of this prescribing information.

Warning

Cases of life-threatening hepatic failure have been reported in patients treated with nefazodone hydrochloride tablets. The reported rate in the United States is about 1 case of liver failure resulting in death or transplant per 250,000 to 300,000 patient-years of nefazodone hydrochloride treatment. The total patient-years is a summation of each patient’s duration of exposure expressed in years. For example, 1 patient-year is equal to 2 patients each treated for 6 months, 3 patients each treated for 4 months, etc. (see WARNINGS).

Ordinarily, treatment with nefazodone hydrochloride tablets should not be initiated in individuals with active liver disease or with elevated baseline serum transaminases. There is no evidence that pre-existing liver disease increases the likelihood of developing liver failure, however, baseline abnormalities can complicate patient monitoring.

Patients should be advised to be alert for signs and symptoms of liver dysfunction (jaundice, anorexia, gastrointestinal complaints, malaise, etc.) and to report them to their doctor immediately if they occur.

Nefazodone hydrochloride tablets should be discontinued if clinical signs or symptoms suggest liver failure (see PRECAUTIONS, Information for Patients). Patients who develop evidence of hepatocellular injury such as increased serum AST or serum ALT levels ≥ 3 times the upper limit of NORMAL, while on nefazodone hydrochloride tablets should be withdrawn from the drug. These patients should be presumed to be at increased risk for liver injury if nefazodone hydrochloride is reintroduced. Accordingly, such patients should not be considered for re-treatment.

DESCRIPTION

Nefazodone hydrochloride tablets, USP are an antidepressant for oral administration with a chemical structure unrelated to selective serotonin reuptake inhibitors, tricyclics, tetracyclics, or monoamine oxidase inhibitors (MAOI).

Nefazodone hydrochloride is a synthetically derived phenylpiperazine antidepressant. The chemical name for nefazodone hydrochloride is 2-[3-[4-(3-chlorophenyl)-1-piperazinyl]propyl]-5-ethyl-2,4-dihydro-4-(2-phenoxyethyl)-3H-1,2,4-triazol-3-one monohydrochloride. The structural formula is:

Nefazodone hydrochloride is a nonhygroscopic, white crystalline solid. It is freely soluble in chloroform, soluble in propylene glycol, and slightly soluble in polyethylene glycol and water.

Nefazodone hydrochloride tablets, USP are supplied as capsule-shaped tablets containing 50 mg, 100 mg, 150 mg, 200 mg, or 250 mg of nefazodone hydrochloride, USP and the following inactive ingredients: colloidal silicon dioxide, magnesium stearate, microcrystalline cellulose, sodium starch glycolate and povidone. Additionally, the 50 mg tablets include ferric oxide red as a colorant, the 150 mg tablets include ferric oxide red and yellow as colorants, and the 200 mg tablets include ferric oxide yellow as a colorant.

CLINICAL PHARMACOLOGY

Pharmacodynamics

The mechanism of action of nefazodone, as with other antidepressants, is unknown.

Preclinical studies have shown that nefazodone inhibits neuronal uptake of serotonin and norepinephrine.

Nefazodone occupies central 5-HT2 receptors at nanomolar concentrations, and acts as an antagonist at this receptor. Nefazodone was shown to antagonize alpha1-adrenergic receptors, a property which may be associated with postural hypotension. In vitro binding studies showed that nefazodone had no significant affinity for the following receptors: alpha2 and beta adrenergic, 5-HT1A, cholinergic, dopaminergic, or benzodiazepine.

Pharmacokinetics

Nefazodone is rapidly and completely absorbed but is subject to extensive metabolism, so that its absolute bioavailability is low, about 20%, and variable. Peak plasma concentrations occur at about one hour and the half-life of nefazodone is 2 to 4 hours.

Both nefazodone and its pharmacologically similar metabolite, hydroxynefazodone, exhibit nonlinear kinetics for both dose and time, with AUC and Cmax increasing more than proportionally with dose increases and more than expected upon multiple dosing over time, compared to single dosing. For example, in a multiple-dose study involving BID dosing with 50, 100, and 200 mg, the AUC for nefazodone and hydroxynefazodone increased by about 4 fold with an increase in dose from 200 to 400 mg per day; Cmax increased by about 3 fold with the same dose increase. In a multiple-dose study involving BID dosing with 25, 50, 100, and 150 mg, the accumulation ratios for nefazodone and hydroxynefazodone AUC, after 5 days of BID dosing relative to the first dose, ranged from approximately 3 to 4 at the lower doses (50 to 100 mg/day) and from 5 to 7 at the higher doses (200 to 300 mg/day); there were also approximately 2 to 4 fold increases in Cmax after 5 days of BID dosing relative to the first dose, suggesting extensive and greater than predicted accumulation of nefazodone and its hydroxy metabolite with multiple dosing. Steady-state plasma nefazodone and metabolite concentrations are attained within 4 to 5 days of initiation of BID dosing or upon dose increase or decrease.

Nefazodone is extensively metabolized after oral administration by n-dealkylation and aliphatic and aromatic hydroxylation, and less than 1% of administered nefazodone is excreted unchanged in urine. Attempts to characterize three metabolites identified in plasma, hydroxynefazodone (HO-NEF), meta-chlorophenylpiperazine (mCPP), and a triazole-dione metabolite, have been carried out. The AUC (expressed as a multiple of the AUC for nefazodone dosed at 100 mg BID) and elimination half-lives for these three metabolites were as follows:

AUC Multiples and T1/2 for Three Metabolites of Nefazodone (100 mg BID)
Metabolite | AUC Multiple | T1/2
HO-NEF | 0.4 | 1.5 to 4 h
mCPP | 0.07 | 4 to 8 h
Triazole-dione | 4.0 | 18 h

HO-NEF possesses a pharmacological profile qualitatively and quantitatively similar to that of nefazodone. mCPP has some similarities to nefazodone, but also has agonist activity at some serotonergic receptor subtypes. The pharmacological profile of the triazole-dione metabolite has not yet been well characterized. In addition to the above compounds, several other metabolites were present in plasma but have not been tested for pharmacological activity.

After oral administration of radiolabeled nefazodone, the mean half-life of total label ranged between 11 and 24 hours. Approximately 55% of the administered radioactivity was detected in urine and about 20 to 30% in feces.

Distribution

Nefazodone is widely distributed in body tissues, including the central nervous system (CNS). In humans the volume of distribution of nefazodone ranges from 0.22 to 0.87 L/kg.

Protein Binding

At concentrations of 25 to 2500 ng/mL nefazodone is extensively (> 99%) bound to human plasma proteins in vitro. The administration of 200 mg BID of nefazodone for 1 week did not increase the fraction of unbound warfarin in subjects whose prothrombin times had been prolonged by warfarin therapy to 120 to 150% of the laboratory control (see PRECAUTIONS, Drug Interactions). While nefazodone did not alter the in vitro protein binding of chlorpromazine, desipramine, diazepam, diphenylhydantoin, lidocaine, prazosin, propranolol, or verapamil, it is unknown whether displacement of either nefazodone or these drugs occurs in vivo. There was a 5% decrease in the protein binding of haloperidol; this is probably of no clinical significance.

Effect of Food

Food delays the absorption of nefazodone and decreases the bioavailability of nefazodone by approximately 20%.

Renal Disease

In studies involving 29 renally impaired patients, renal impairment (creatinine clearances ranging from 7 to 60 mL/min/1.73 m^2) had no effect on steady-state nefazodone plasma concentrations.

Liver Disease

In a multiple-dose study of patients with liver cirrhosis, the AUC values for nefazodone and HO-NEF at steady state were approximately 25% greater than those observed in normal volunteers.

Age/Gender Effects

After single doses of 300 mg to younger (18 to 45 years) and older patients (> 65 years), Cmax and AUC for nefazodone and hydroxynefazodone were up to twice as high in the older patients. With multiple doses, however, differences were much smaller, 10 to 20%. A similar result was seen for gender, with a higher Cmax and AUC in women after single doses but no difference after multiple doses.

Treatment with nefazodone should be initiated at half the usual dose in elderly patients, especially women (see DOSAGE AND ADMINISTRATION), but the therapeutic dose range is similar in younger and older patients.

Clinical Efficacy Trial Results

Studies in Outpatients with Depression

During its premarketing development, the efficacy of nefazodone was evaluated at doses within the therapeutic range in five well-controlled, short-term (6 to 8 weeks) clinical investigations. These trials enrolled outpatients meeting DSM-III or DSM-IIIR criteria for major depression. Among these trials, two demonstrated the effectiveness of nefazodone, and two provided additional support for that conclusion.

One trial was a 6 week dose-titration study comparing nefazodone in two dose ranges (up to 300 mg/day and up to 600 mg/day [mean modal dose for this group was about 400 mg/day], on a BID schedule) and placebo. The second trial was an 8 week dose-titration study comparing nefazodone (up to 600 mg/day; mean modal dose was 375 mg/day), imipramine (up to 300 mg/day), and placebo, all on a BID schedule. Both studies demonstrated nefazodone, at doses titrated between 300 mg to 600 mg/day (therapeutic dose range), to be superior to placebo on at least three of the following four measures: 17 Item Hamilton Depression Rating Scale or HDRS (total score), Hamilton Depressed Mood item, Clinical Global Impressions (CGI) Severity score, and CGI Improvement score. Significant differences were also found for certain factors of the HDRS (e.g., anxiety factor, sleep disturbance factor, and retardation factor). In the two supportive studies, nefazodone was titrated up to 500 or 600 mg/day (mean modal doses of 462 mg/day and 363 mg/day). In the fifth study, the differentiation in response rates between nefazodone and placebo was not statistically significant. Three additional trials were conducted using subtherapeutic doses of nefazodone.

Overall, approximately two thirds of patients in these trials were women, and an analysis of the effects of gender on outcome did not suggest any differential responsiveness on the basis of sex. There were too few elderly patients in these trials to reveal possible age-related differences in response.

Since its initial marketing as an antidepressant drug product, additional clinical investigations of nefazodone have been conducted. These studies explored nefazodone’s use under conditions not evaluated fully at the time initial marketing approval was granted.

Studies in “Inpatients”

Two studies were conducted to evaluate nefazodone’s effectiveness in hospitalized depressed patients. These were 6 week, dose-titration trials comparing nefazodone (up to 600 mg/day) and placebo, on a BID schedule. In one study, nefazodone was superior to placebo. In this study, the mean modal dose of nefazodone was 503 mg/day, and 85% of these inpatients were melancholic; at baseline, patients were distributed at the higher end of the 7 point CGI Severity scale, as follows: 4 = moderately ill (17%); 5 = markedly ill (48%); 6 = severely ill (32%). In the other study, the differentiation in response rates between nefazodone and placebo was not statistically significant. This result may be explained by the “high” rate of spontaneous improvement among the patients randomized to placebo.

Studies of “Relapse Prevention in Patients Recently Recovered (Clinically) From Depression”

Two studies were conducted to assess nefazodone’s capacity to maintain a clinical remission in acutely depressed patients who were judged to have responded adequately (HDRS total score ≤ 10) after a 16 week period of open treatment with nefazodone (titration up to 600 mg/day). In one study, nefazodone was superior to placebo. In this study, patients (n = 131) were randomized to continuation on nefazodone or placebo for an additional 36 weeks (1 year total). This study demonstrated a significantly lower relapse rate (HDRS total score ≥ 18) for patients taking nefazodone compared to those on placebo. The second study was of appropriate design and power, but the sample of patients admitted for evaluation did not suffer relapses at a high enough incidence to provide a meaningful test of nefazodone’s efficacy for this use.

Comparisons of Clinical Trial Results

Highly variable results have been seen in the clinical development of all antidepressant drugs. Furthermore, in those circumstances when the drugs have not been studied in the same controlled clinical trial(s), comparisons among the findings of studies evaluating the effectiveness of different antidepressant drug products are inherently unreliable. Because conditions of testing (e.g., patient samples, investigators, doses of the treatments administered and compared, outcome measures, etc.) vary among trials, it is virtually impossible to distinguish a difference in drug effect from a difference due to one or more of the confounding factors just enumerated.

INDICATIONS AND USAGE

Nefazodone hydrochloride tablets are indicated for the treatment of depression. When deciding among the alternative treatments available for this condition, the prescriber should consider the risk of hepatic failure associated with nefazodone hydrochloride treatment (see WARNINGS). In many cases, this would lead to the conclusion that other drugs should be tried first.

The efficacy of nefazodone in the treatment of depression was established in 6 to 8 week controlled trials of outpatients and in a 6 week controlled trial of depressed inpatients whose diagnoses corresponded most closely to the DSM-III or DSM-IIIR category of major depressive disorder (see CLINICAL PHARMACOLOGY).

A major depressive episode implies a prominent and relatively persistent depressed or dysphoric mood that usually interferes with daily functioning (nearly every day for at least 2 weeks). It must include either depressed mood or loss of interest or pleasure and at least five of the following nine symptoms: depressed mood, loss of interest in usual activities, significant change in weight and/or appetite, insomnia or hypersomnia, psychomotor agitation or retardation, increased fatigue, feelings of guilt or worthlessness, slowed thinking or impaired concentration, a suicide attempt or suicidal ideation.

The efficacy of nefazodone in reducing relapse in patients with major depression who were judged to have had a satisfactory clinical response to 16 weeks of open-label nefazodone treatment for an acute depressive episode has been demonstrated in a randomized placebo-controlled trial (see CLINICAL PHARMACOLOGY). Although remitted patients were followed for as long as 36 weeks in the study cited (i.e., 52 weeks total), the physician who elects to use nefazodone for extended periods should periodically reevaluate the long-term usefulness of the drug for the individual patient.

CONTRAINDICATIONS

Coadministration of terfenadine, astemizole, cisapride, pimozide, or carbamazepine with nefazodone hydrochloride is contraindicated (see WARNINGSand PRECAUTIONS).

Nefazodone hydrochloride tablets are contraindicated in patients who were withdrawn from nefazodone because of evidence of liver injury (see BOXED WARNING). Nefazodone hydrochloride tablets are also contraindicated in patients who have demonstrated hypersensitivity to nefazodone hydrochloride, its inactive ingredients, or other phenylpiperazine antidepressants.

The coadministration of triazolam and nefazodone causes a significant increase in the plasma level of triazolam (see WARNINGSand PRECAUTIONS), and a 75% reduction in the initial triazolam dosage is recommended if the two drugs are to be given together. Because not all commercially available dosage forms of triazolam permit a sufficient dosage reduction, the coadministration of triazolam and nefazodone should be avoided for most patients, including the elderly.

WARNINGS

Clinical Worsening and Suicide Risk

Patients with major depressive disorder (MDD), both adult and pediatric, may experience worsening of their depression and/or the emergence of suicidal ideation and behavior (suicidality) or unusual changes in behavior, whether or not they are taking antidepressant medications, and this risk may persist until significant remission occurs. Suicide is a known risk of depression and certain other psychiatric disorders, and these disorders themselves are the strongest predictors of suicide. There has been a long-standing concern, however, that antidepressants may have a role in inducing worsening of depression and the emergence of suicidality in certain patients during the early phases of treatment. Pooled analyses of short-term placebo-controlled trials of antidepressant drugs (SSRIs and others) showed that these drugs increase the risk of suicidal thinking and behavior (suicidality) in children, adolescents, and young adults (ages 18 to 24) with major depressive disorder (MDD) and other psychiatric disorders. Short-term studies did not show an increase in the risk of suicidality with antidepressants compared to placebo in adults beyond age 24; there was a reduction with antidepressants compared to placebo in adults aged 65 and older.

The pooled analyses of placebo-controlled trials in children and adolescents with MDD, obsessive compulsive disorder (OCD), or other psychiatric disorders included a total of 24 short-term trials of 9 antidepressant drugs in over 4400 patients. The pooled analyses of placebo-controlled trials in adults with MDD or other psychiatric disorders included a total of 295 short-term trials (median duration of 2 months) of 11 antidepressant drugs in over 77,000 patients. There was considerable variation in risk of suicidality among drugs, but a tendency toward an increase in the younger patients for almost all drugs studied. There were differences in absolute risk of suicidality across the different indications, with the highest incidence in MDD. The risk differences (drug vs placebo), however, were relatively stable within age strata and across indications. These risk differences (drug-placebo difference in the number of cases of suicidality per 1000 patients treated) are provided in Table 1.

Table 1
Age Range | Drug-Placebo Difference in Number of Cases of Suicidality per 1000 Patients Treated
 | Increases Compared to Placebo
< 18 | 14 additional cases
18 to 24 | 5 additional cases
 | Decreases Compared to Placebo
25 to 64 | 1 fewer case
≥ 65 | 6 fewer cases

No suicides occurred in any of the pediatric trials. There were suicides in the adult trials, but the number was not sufficient to reach any conclusion about drug effect on suicide.

It is unknown whether the suicidality risk extends to longer-term use, i.e., beyond several months. However, there is substantial evidence from placebo-controlled maintenance trials in adults with depression that the use of antidepressants can delay the recurrence of depression.

All patients being treated with antidepressants for any indication should be monitored appropriately and observed closely for clinical worsening, suicidality, and unusual changes in behavior, especially during the initial few months of a course of drug therapy, or at times of dose changes, either increases or decreases.

The following symptoms, anxiety, agitation, panic attacks, insomnia, irritability, hostility, aggressiveness, impulsivity, akathisia (psychomotor restlessness), hypomania, and mania, have been reported in adult and pediatric patients being treated with antidepressants for major depressive disorder as well as for other indications, both psychiatric and nonpsychiatric. Although a causal link between the emergence of such symptoms and either the worsening of depression and/or the emergence of suicidal impulses has not been established, there is concern that such symptoms may represent precursors to emerging suicidality.

Consideration should be given to changing the therapeutic regimen, including possibly discontinuing the medication, in patients whose depression is persistently worse, or who are experiencing emergent suicidality or symptoms that might be precursors to worsening depression or suicidality, especially if these symptoms are severe, abrupt in onset, or were not part of the patient's presenting symptoms.

Families and caregivers of patients being treated with antidepressants for major depressive disorder or other indications, both psychiatric and nonpsychiatric, should be alerted about the need to monitor patients for the emergence of agitation, irritability, unusual changes in behavior, and the other symptoms described above, as well as the emergence of suicidality, and to report such symptoms immediately to health care providers. Such monitoring should include daily observation by families and caregivers. Prescriptions for nefazodone hydrochloride tablets should be written for the smallest quantity of tablets consistent with good patient management, in order to reduce the risk of overdose.

Screening Patients for Bipolar Disorder

A major depressive episode may be the initial presentation of bipolar disorder. It is generally believed (though not established in controlled trials) that treating such an episode with an antidepressant alone may increase the likelihood of precipitation of a mixed/manic episode in patients at risk for bipolar disorder. Whether any of the symptoms described above represent such a conversion is unknown. However, prior to initiating treatment with an antidepressant, patients with depressive symptoms should be adequately screened to determine if they are at risk for bipolar disorder; such screening should include a detailed psychiatric history, including a family history of suicide, bipolar disorder, and depression. It should be noted that nefazodone hydrochloride tablets are not approved for use in treating bipolar depression.

Angle-Closure Glaucoma

The pupillary dilation that occurs following use of many antidepressant drugs including nefazodone hydrochloride tablets may trigger an angle closure attack in a patient with anatomically narrow angles who does not have a patent iridectomy.

Hepatotoxicity

(See BOXED WARNING.)

Cases of life-threatening hepatic failure have been reported in patients treated with nefazodone hydrochloride tablets.

The reported rate in the United States is about 1 case of liver failure resulting in death or transplant per 250,000 to 300,000 patient-years of nefazodone treatment. This represents a rate of about 3 to 4 times the estimated background rate of liver failure. This rate is an underestimate because of under reporting, and the true risk could be considerably greater than this. A large cohort study of antidepressant users found no cases of liver failure leading to death or transplant among nefazodone users in about 30,000 patient-years of exposure. The spontaneous report data and the cohort study results provide estimates of the upper and lower limits of the risk of liver failure in nefazodone-treated patients, but are not capable of providing a precise risk estimate.

The time to liver injury for the reported liver failure cases resulting in death or transplant generally ranged from 2 weeks to 6 months on nefazodone therapy. Although some reports described dark urine and nonspecific prodromal symptoms (e.g., anorexia, malaise, and gastrointestinal symptoms), other reports did not describe the onset of clear prodromal symptoms prior to the onset of jaundice.

The physician may consider the value of liver function testing. Periodic serum transaminase testing has not been proven to prevent serious injury but it is generally believed that early detection of drug-induced hepatic injury along with immediate withdrawal of the suspect drug enhances the likelihood for recovery.

Patients should be advised to be alert for signs and symptoms of liver dysfunction (jaundice, anorexia, gastrointestinal complaints, malaise, etc.) and to report them to their doctor immediately if they occur. Ongoing clinical assessment of patients should govern physician interventions, including diagnostic evaluations and treatment.

Nefazodone should be discontinued if clinical signs or symptoms suggest liver failure (see PRECAUTIONS, Information for Patients). Patients who develop evidence of hepatocellular injury such as increased serum AST or serum ALT levels ≥ 3 times the upper limit of NORMAL, while on nefazodone should be withdrawn from the drug. These patients should be presumed to be at increased risk for liver injury if nefazodone is reintroduced. Accordingly, such patients should not be considered for re-treatment.

Potential for Interaction with Monoamine Oxidase Inhibitors

In patients receiving antidepressants with pharmacological properties similar to nefazodone in combination with a monoamine oxidase inhibitor (MAOI), there have been reports of serious, sometimes fatal, reactions. For a selective serotonin reuptake inhibitor (SSRI), these reactions have included hyperthermia, rigidity, myoclonus, autonomic instability with possible rapid fluctuations of vital signs, and mental status changes that include extreme agitation progressing to delirium and coma. These reactions have also been reported in patients who have recently discontinued that drug and have been started on an MAOI. Some cases presented with features resembling neuroleptic malignant syndrome. Severe hyperthermia and seizures, sometimes fatal, have been reported in association with the combined use of tricyclic antidepressants and MAOIs. These reactions have also been reported in patients who have recently discontinued these drugs and have been started on an MAOI.

Although the effects of combined use of nefazodone and MAOI have not been evaluated in humans or animals, because nefazodone is an inhibitor of both serotonin and norepinephrine reuptake, it is recommended that nefazodone not be used in combination with an MAOI, or within 14 days of discontinuing treatment with an MAOI. At least 1 week should be allowed after stopping nefazodone before starting an MAOI.

Interaction with Triazolobenzodiazepines

Interaction studies of nefazodone with two triazolobenzodiazepines, i.e., triazolam and alprazolam, metabolized by cytochrome P450 3A4, have revealed substantial and clinically important increases in plasma concentrations of these compounds when administered concomitantly with nefazodone.

Triazolam

When a single oral 0.25 mg dose of triazolam was coadministered with nefazodone (200 mg BID) at steady state, triazolam half-life and AUC increased 4 fold and peak concentrations increased 1.7 fold. Nefazodone plasma concentrations were unaffected by triazolam. Coadministration of nefazodone potentiated the effects of triazolam on psychomotor performance tests. If triazolam is coadministered with nefazodone, a 75% reduction in the initial triazolam dosage is recommended. Because not all commercially available dosage forms of triazolam permit sufficient dosage reduction, coadministration of triazolam with nefazodone should be avoided for most patients, including the elderly. In the exceptional case where coadministration of triazolam with nefazodone may be considered appropriate, only the lowest possible dose of triazolam should be used (see CONTRAINDICATIONSand PRECAUTIONS).

Alprazolam

When alprazolam (1 mg BID) and nefazodone (200 mg BID) were coadministered, steady-state peak concentrations, AUC and half-life values for alprazolam increased by approximately 2 fold. Nefazodone plasma concentrations were unaffected by alprazolam. If alprazolam is coadministered with nefazodone, a 50% reduction in the initial alprazolam dosage is recommended. No dosage adjustment is required for nefazodone.

Potential Terfenadine, Astemizole, Cisapride, and Pimozide Interactions

Terfenadine, astemizole, cisapride, and pimozide are all metabolized by the cytochrome P450 3A4 (CYP3A4) isozyme, and it has been demonstrated that ketoconazole, erythromycin, and other inhibitors of CYP3A4 can block the metabolism of these drugs, which can result in increased plasma concentrations of parent drug. Increased plasma concentrations of terfenadine, astemizole, cisapride, and pimozide are associated with QT prolongation and with rare cases of serious cardiovascular adverse events, including death, due principally to ventricular tachycardia of the torsade de pointes type. Nefazodone has been shown in vitro to be an inhibitor of CYP3A4. Consequently, it is recommended that nefazodone not be used in combination with either terfenadine, astemizole, cisapride, or pimozide (see CONTRAINDICATIONSand PRECAUTIONS).

Interaction with Carbamazepine

The coadministration of carbamazepine 200 mg BID with nefazodone 200 mg BID, at steady state for both drugs, resulted in almost 95% reductions in AUCs for nefazodone and hydroxynefazodone, likely resulting in insufficient plasma nefazodone and hydroxynefazodone concentrations for achieving an antidepressant effect for nefazodone. Consequently, it is recommended that nefazodone not be used in combination with carbamazepine (see CONTRAINDICATIONSand PRECAUTIONS).

PRECAUTIONS

General

Hepatotoxicity

(See BOXED WARNING.)

Postural Hypotension

A pooled analysis of the vital signs monitored during placebo-controlled premarketing studies revealed that 5.1% of nefazodone patients compared to 2.5% of placebo patients (p ≤ 0.01) met criteria for a potentially important decrease in blood pressure at some time during treatment (systolic blood pressure ≤ 90 mmHg and a change from baseline of ≥ 20 mmHg). While there was no difference in the proportion of nefazodone and placebo patients having adverse events characterized as ‘syncope’ (nefazodone, 0.2%; placebo, 0.3%), the rates for adverse events characterized as ‘postural hypotension’ were as follows: nefazodone (2.8%), tricyclic antidepressants (10.9%), SSRI (1.1%), and placebo (0.8%). Thus, the prescriber should be aware that there is some risk of postural hypotension in association with nefazodone use. Nefazodone should be used with caution in patients with known cardiovascular or cerebrovascular disease that could be exacerbated by hypotension (history of myocardial infarction, angina, or ischemic stroke) and conditions that would predispose patients to hypotension (dehydration, hypovolemia, and treatment with antihypertensive medication).

Activation of Mania/Hypomania

During premarketing testing, hypomania or mania occurred in 0.3% of nefazodone-treated unipolar patients, compared to 0.3% of tricyclic- and 0.4% of placebo-treated patients. In patients classified as bipolar the rate of manic episodes was 1.6% for nefazodone, 5.1% for the combined tricyclic-treated groups, and 0% for placebo-treated patients. Activation of mania/hypomania is a known risk in a small proportion of patients with major affective disorder treated with other marketed antidepressants. As with all antidepressants, nefazodone should be used cautiously in patients with a history of mania.

Seizures

During premarketing testing, a recurrence of a petit mal seizure was observed in a patient receiving nefazodone who had a history of such seizures. In addition, one nonstudy participant reportedly experienced a convulsion (type not documented) following a multiple-drug overdose (see OVERDOSAGE). Rare occurrences of convulsions (including grand mal seizures) following nefazodone administration have been reported since market introduction. A causal relationship to nefazodone has not been established (see ADVERSE REACTIONS).

Priapism

While priapism did not occur during premarketing experience with nefazodone, rare reports of priapism have been received since market introduction. A causal relationship to nefazodone has not been established (see ADVERSE REACTIONS). If patients present with prolonged or inappropriate erections, they should discontinue therapy immediately and consult their physicians. If the condition persists for more than 24 hours, a urologist should be consulted to determine appropriate management.

Use in Patients with Concomitant Illness

Nefazodone has not been evaluated or used to any appreciable extent in patients with a recent history of myocardial infarction or unstable heart disease. Patients with these diagnoses were systematically excluded from clinical studies during the product’s premarketing testing. Evaluation of electrocardiograms of 1153 patients who received nefazodone in 6 to 8 week, double-blind, placebo-controlled trials did not indicate that nefazodone is associated with the development of clinically important ECG abnormalities. However, sinus bradycardia, defined as heart rate ≤ 50 bpm and a decrease of at least 15 bpm from baseline, was observed in 1.5% of nefazodone-treated patients compared to 0.4% of placebo-treated patients (p ≤ 0.05). Because patients with a recent history of myocardial infarction or unstable heart disease were excluded from clinical trials, such patients should be treated with caution.

In patients with cirrhosis of the liver, AUC values of nefazodone and HO-NEF were increased by approximately 25%.

Information for Patients (see Patient Information)

Prescribers or other health professionals should inform patients, their families, and their caregivers about the benefits and risks associated with treatment with nefazodone hydrochloride tablets and should counsel them in its appropriate use. A patient Medication Guide about “Antidepressant Medicines, Depression and other Serious Mental Illnesses, and Suicidal Thoughts or Actions” is available for nefazodone hydrochloride tablets. The prescriber or health professional should instruct patients, their families, and their caregivers to read the Medication Guide and should assist them in understanding its contents. Patients should be given the opportunity to discuss the contents of the Medication Guide and to obtain answers to any questions they may have. The complete text of the Medication Guide is reprinted at the end of this document.

Patients should be advised of the following issues and asked to alert their prescriber if these occur while taking nefazodone hydrochloride tablets.

Clinical Worsening and Suicide Risk

Patients, their families, and their caregivers should be encouraged to be alert to the emergence of anxiety, agitation, panic attacks, insomnia, irritability, hostility, aggressiveness, impulsivity, akathisia (psychomotor restlessness), hypomania, mania, other unusual changes in behavior, worsening of depression, and suicidal ideation, especially early during antidepressant treatment and when the dose is adjusted up or down. Families and caregivers of patients should be advised to look for the emergence of such symptoms on a day-to-day basis, since changes may be abrupt. Such symptoms should be reported to the patient's prescriber or health professional, especially if they are severe, abrupt in onset, or were not part of the patient's presenting symptoms. Symptoms such as these may be associated with an increased risk for suicidal thinking and behavior and indicate a need for very close monitoring and possibly changes in the medication.

Hepatotoxicity

Patients should be informed that nefazodone therapy has been associated with liver abnormalities ranging from asymptomatic reversible serum transaminase increases to cases of liver failure resulting in transplant and/or death. At present, there is no way to predict who is likely to develop liver failure. Ordinarily, patients with active liver disease should not be treated with nefazodone. Patients should be advised to be alert for signs of liver dysfunction (jaundice, anorexia, gastrointestinal complaints, malaise, etc.) and to report them to their doctor immediately if they occur.

Time to Response/Continuation

As with all antidepressants, several weeks on treatment may be required to obtain the full antidepressant effect. Once improvement is noted, it is important for patients to continue drug treatment as directed by their physician.

Interference with Cognitive and Motor Performance

Since any psychoactive drug may impair judgment, thinking, or motor skills, patients should be cautioned about operating hazardous machinery, including automobiles, until they are reasonably certain that nefazodone therapy does not adversely affect their ability to engage in such activities.

Pregnancy

Patients should be advised to notify their physician if they become pregnant or intend to become pregnant during therapy.

Nursing

Patients should be advised to notify their physician if they are breast-feeding an infant (see PRECAUTIONS, Nursing Mothers).

Concomitant Medication

Patients should be advised to inform their physicians if they are taking, or plan to take, any prescription or over-the-counter drugs, since there is a potential for interactions. Significant caution is indicated if nefazodone is to be used in combination with XANAX® (alprazolam), concomitant use with HALCION® (triazolam) should be avoided for most patients including the elderly, and concomitant use with SELDANE® (terfenadine), HISMANAL® (astemizole), PROPULSID® (cisapride), ORAP® (pimozide), or TEGRETOL® (carbamazepine) is contraindicated (see CONTRAINDICATIONSand WARNINGS).

Alcohol

Patients should be advised to avoid alcohol while taking nefazodone.

Allergic Reactions

Patients should be advised to notify their physician if they develop a rash, hives, or a related allergic phenomenon.

Visual Disturbances

There have been reports of visual disturbances associated with the use of nefazodone, including blurred vision, scotoma, and visual trails. Patients should be advised to notify their physician if they develop visual disturbances (see ADVERSE REACTIONS).

Patients should be advised that taking nefazodone hydrochloride tablets can cause mild pupillary dilation, which in susceptible individuals, can lead to an episode of angle-closure glaucoma. Pre-existing glaucoma is almost always open-angle glaucoma because angle-closure glaucoma, when diagnosed, can be treated definitively with iridectomy. Open-angle glaucoma is not a risk factor for angle closure glaucoma. Patients may wish to be examined to determine whether they are susceptible to angle closure, and have a prophylactic procedure (e.g., iridectomy), if they are susceptible.

Laboratory Tests

There are no specific laboratory tests recommended.

Drug Interactions

Drugs Highly Bound to Plasma Protein

Because nefazodone is highly bound to plasma protein (see CLINICAL PHARMACOLOGY, Pharmacokinetics), administration of nefazodone to a patient taking another drug that is highly protein bound may cause increased free concentrations of the other drug, potentially resulting in adverse events. Conversely, adverse effects could result from displacement of nefazodone by other highly bound drugs.

Warfarin – There were no effects on the prothrombin or bleeding times or upon the pharmacokinetics of R-warfarin when nefazodone (200 mg BID) was administered for 1 week to subjects who had been pretreated for 2 weeks with warfarin. Although the coadministration of nefazodone did decrease the subjects’ exposure to S-warfarin by 12%, the lack of effects on the prothrombin and bleeding times indicates this modest change is not clinically significant. Although these results suggest no adjustments in warfarin dosage are required when nefazodone is administered to patients stabilized on warfarin, such patients should be monitored as required by standard medical practices.

CNS-Active Drugs

Monoamine Oxidase Inhibitors – See WARNINGS.

Haloperidol – When a single oral 5 mg dose of haloperidol was coadministered with nefazodone (200 mg BID) at steady state, haloperidol apparent clearance decreased by 35% with no significant increase in peak haloperidol plasma concentrations or time of peak. This change is of unknown clinical significance. Pharmacodynamic effects of haloperidol were generally not altered significantly. There were no changes in the pharmacokinetic parameters for nefazodone. Dosage adjustment of haloperidol may be necessary when coadministered with nefazodone.

Lorazepam – When lorazepam (2 mg BID) and nefazodone (200 mg BID) were coadministered to steady state, there was no change in any pharmacokinetic parameter for either drug compared to each drug administered alone. Therefore, dosage adjustment is not necessary for either drug when coadministered.

Triazolam/Alprazolam – See CONTRAINDICATIONSand WARNINGS.

Alcohol – Although nefazodone did not potentiate the cognitive and psychomotor effects of alcohol in experiments with normal subjects, the concomitant use of nefazodone and alcohol in depressed patients is not advised.

Buspirone – In a study of steady-state pharmacokinetics in healthy volunteers, coadministration of buspirone (2.5 or 5 mg BID) with nefazodone (250 mg BID) resulted in marked increases in plasma buspirone concentrations (increases up to 20 fold in Cmax and up to 50 fold in AUC) and statistically significant decreases (about 50%) in plasma concentrations of the buspirone metabolite 1-pyrimidinylpiperazine. With 5 mg BID doses of buspirone, slight increases in AUC were observed for nefazodone (23%) and its metabolites hydroxynefazodone (17%) and mCPP (9%). Subjects receiving nefazodone 250 mg BID and buspirone 5 mg BID experienced lightheadedness, asthenia, dizziness, and somnolence, adverse events also observed with either drug alone. If the two drugs are to be used in combination, a low dose of buspirone (e.g., 2.5 mg QD) is recommended. Subsequent dose adjustment of either drug should be based on clinical assessment.

Pimozide – See CONTRAINDICATIONS, WARNINGS, and PRECAUTIONS, Pharmacokinetics of Nefazodone in ‘Poor Metabolizers’ and Potential Interaction With Drugs That Inhibit and/or Are Metabolized by Cytochrome P450 Isozymes.

Fluoxetine – When fluoxetine (20 mg QD) and nefazodone (200 mg BID) were administered at steady state there were no changes in the pharmacokinetic parameters for fluoxetine or its metabolite, norfluoxetine. Similarly, there were no changes in the pharmacokinetic parameters of nefazodone or HO-NEF; however, the mean AUC levels of the nefazodone metabolites mCPP and triazole-dione increased by 3 to 6 fold and 1.3 fold, respectively. When a 200 mg dose of nefazodone was administered to subjects who had been receiving fluoxetine for 1 week, there was an increased incidence of transient adverse events such as headache, lightheadedness, nausea, or paresthesia, possibly due to the elevated mCPP levels. Patients who are switched from fluoxetine to nefazodone without an adequate washout period may experience similar transient adverse events. The possibility of this happening can be minimized by allowing a washout period before initiating nefazodone therapy and by reducing the initial dose of nefazodone. Because of the long half-life of fluoxetine and its metabolites, this washout period may range from one to several weeks depending on the dose of fluoxetine and other individual patient variables.

Phenytoin – Pretreatment for 7 days with 200 mg BID of nefazodone had no effect on the pharmacokinetics of a single 300 mg oral dose of phenytoin. However, due to the nonlinear pharmacokinetics of phenytoin, the failure to observe a significant effect on the single-dose pharmacokinetics of phenytoin does not preclude the possibility of a clinically significant interaction with nefazodone when phenytoin is dosed chronically. However, no change in the initial dosage of phenytoin is considered necessary and any subsequent adjustment of phenytoin dosage should be guided by usual clinical practices.

Desipramine – When nefazodone (150 mg BID) and desipramine (75 mg QD) were administered together there were no changes in the pharmacokinetics of desipramine or its metabolite, 2-hydroxy desipramine. There were also no changes in the pharmacokinetics of nefazodone or its triazole-dione metabolite, but the AUC and Cmax of mCPP increased by 44% and 48%, respectively, while the AUC of HO-NEF decreased by 19%. No changes in doses of either nefazodone or desipramine are necessary when the two drugs are given concomitantly. Subsequent dose adjustments should be made on the basis of clinical response.

Lithium – In 13 healthy subjects the coadministration of nefazodone (200 mg BID) with lithium (500 mg BID) for 5 days (steady-state conditions) was found to be well tolerated. When the two drugs were coadministered, there were no changes in the steady-state pharmacokinetics of either lithium, nefazodone, or its metabolite HO-NEF; however, there were small decreases in the steady-state plasma concentrations of two nefazodone metabolites, mCPP and triazole-dione, which are considered not to be of clinical significance. Therefore, no dosage adjustment of either lithium or nefazodone is required when they are coadministered.

Carbamazepine – The coadministration of nefazodone (200 mg BID) for 5 days to 12 healthy subjects on carbamazepine who had achieved steady state (200 mg BID) was found to be well tolerated. Steady-state conditions for carbamazepine, nefazodone, and several of their metabolites were achieved by day 5 of coadministration. With coadministration of the two drugs there were significant increases in the steady-state Cmax and AUC of carbamazepine (23% and 23%, respectively), while the steady-state Cmax and the AUC of the carbamazepine metabolite, 10,11 epoxycarbamazepine, decreased by 21% and 20%, respectively. The coadministration of the two drugs significantly reduced the steady-state Cmax and AUC of nefazodone by 86% and 93%, respectively. Similar reductions in the Cmax and AUC of HO-NEF were also observed (85% and 94%), while the reductions in Cmax and AUC of mCPP and triazole-dione were more modest (13% and 44% for the former and 28% and 57% for the latter). Due to the potential for coadministration of carbamazepine to result in insufficient plasma nefazodone and hydroxynefazodone concentrations for achieving an antidepressant effect for nefazodone, it is recommended that nefazodone not be used in combination with carbamazepine (see CONTRAINDICATIONSand WARNINGS).

General Anesthetics – Little is known about the potential for interaction between nefazodone and general anesthetics; therefore, prior to elective surgery, nefazodone hydrochloride should be discontinued for as long as clinically feasible.

Other CNS-Active Drugs – The use of nefazodone in combination with other CNS-active drugs has not been systematically evaluated. Consequently, caution is advised if concomitant administration of nefazodone and such drugs is required.

Cimetidine

When nefazodone (200 mg BID) and cimetidine (300 mg QID) were coadministered for one week, no change in the steady-state pharmacokinetics of either nefazodone or cimetidine was observed compared to each dosed alone. Therefore, dosage adjustment is not necessary for either drug when coadministered.

Theophylline

When nefazodone (200 mg BID) was given to patients being treated with theophylline (600 to 1200 mg/day) for chronic obstructive pulmonary disease, there was no change in the steady-state pharmacokinetics of either nefazodone or theophylline. FEV1 measurements taken when theophylline and nefazodone were coadministered did not differ from baseline dosage (i.e., when theophylline was administered alone). Therefore, dosage adjustment is not necessary for either drug when coadministered.

Cardiovascular-Active Drugs

Digoxin – When nefazodone (200 mg BID) and digoxin (0.2 mg QD) were coadministered for 9 days to healthy male volunteers (n = 18) who were phenotyped as CYP2D6 extensive metabolizers, Cmax, Cmin, and AUC of digoxin were increased by 29%, 27%, and 15%, respectively. Digoxin had no effects on the pharmacokinetics of nefazodone and its active metabolites. Because of the narrow therapeutic index of digoxin, caution should be exercised when nefazodone and digoxin are coadministered; plasma level monitoring for digoxin is recommended.

Propranolol – The coadministration of nefazodone (200 mg BID) and propranolol (40 mg BID) for 5.5 days to healthy male volunteers (n = 18), including 3 poor and 15 extensive CYP2D6 metabolizers, resulted in 30% and 14% reductions in Cmax and AUC of propranolol, respectively, and a 14% reduction in Cmax for the metabolite, 4-hydroxypropranolol. The kinetics of nefazodone, hydroxynefazodone, and triazole-dione were not affected by coadministration of propranolol. However, Cmax, Cmin, and AUC of m-chlorophenylpiperazine were increased by 23%, 54%, and 28%, respectively. No change in initial dose of either drug is necessary and dose adjustments should be made on the basis of clinical response.

HMG-CoA Reductase Inhibitors – When single 40 mg doses of simvastatin or atorvastatin, both substrates of CYP3A4, were given to healthy adult volunteers who had received nefazodone hydrochloride, 200 mg BID for 6 days, approximately 20 fold increases in plasma concentrations of simvastatin and simvastatin acid and 3 to 4 fold increases in plasma concentrations of atorvastatin and atorvastatin lactone were seen. These effects appear to be due to the inhibition of CYP3A4 by nefazodone because, in the same study, nefazodone had no significant effect on the plasma concentrations of pravastatin, which is not metabolized by CYP3A4 to a clinically significant extent.

There have been rare reports of rhabdomyolysis involving patients receiving the combination of nefazodone and either simvastatin or lovastatin, also a substrate of CYP3A4 (see ADVERSE REACTIONS, Postintroduction Clinical Experience). Rhabdomyolysis has been observed in patients receiving HMG-CoA reductase inhibitors administered alone (at recommended dosages) and in particular, for certain drugs in this class, when given in combination with inhibitors of the CYP3A4 isozyme.

Caution should be used if nefazodone is administered in combination with HMG-CoA reductase inhibitors that are metabolized by CYP3A4, such as simvastatin, atorvastatin, and lovastatin, and dosage adjustments of these HMG-CoA reductase inhibitors are recommended. Since metabolic interactions are unlikely between nefazodone and HMG-CoA reductase inhibitors that undergo little or no metabolism by the CYP3A4 isozyme, such as pravastatin or fluvastatin, dosage adjustments should not be necessary.

Immunosuppressive Agents

There have been reports of increased blood concentrations of cyclosporine and tacrolimus into toxic ranges when patients received these drugs concomitantly with nefazodone. Both cyclosporine and tacrolimus are substrates of CYP3A4, and nefazodone is known to inhibit this enzyme. If either cyclosporine or tacrolimus is administered with nefazodone, blood concentrations of the immunosuppressive agent should be monitored and dosage adjusted accordingly.

Pharmacokinetics of Nefazodone in ‘Poor Metabolizers’ and Potential Interaction with Drugs That Inhibit and/or Are Metabolized by Cytochrome P450 Isozymes

CYP3A4 Isozyme – Nefazodone has been shown in vitro to be an inhibitor of CYP3A4. This is consistent with the interactions observed between nefazodone and triazolam, alprazolam, buspirone, atorvastatin, and simvastatin, drugs metabolized by this isozyme. Consequently, caution is indicated in the combined use of nefazodone with any drugs known to be metabolized by CYP3A4. In particular, the combined use of nefazodone with triazolam should be avoided for most patients, including the elderly. The combined use of nefazodone with terfenadine, astemizole, cisapride, or pimozide is contraindicated (see CONTRAINDICATIONSand WARNINGS).

CYP2D6 Isozyme – A subset (3% to 10%) of the population has reduced activity of the drug-metabolizing enzyme CYP2D6. Such individuals are referred to commonly as “poor metabolizers” of drugs such as debrisoquin, dextromethorphan, and the tricyclic antidepressants. The pharmacokinetics of nefazodone and its major metabolites are not altered in these “poor metabolizers.” Plasma concentrations of one minor metabolite (mCPP) are increased in this population; the adjustment of nefazodone dosage is not required when administered to “poor metabolizers.” Nefazodone and its metabolites have been shown in vitro to be extremely weak inhibitors of CYP2D6. Thus, it is not likely that nefazodone will decrease the metabolic clearance of drugs metabolized by this isozyme.

CYP1A2 Isozyme – Nefazodone and its metabolites have been shown in vitro not to inhibit CYP1A2. Thus, metabolic interactions between nefazodone and drugs metabolized by this isozyme are unlikely.

Electroconvulsive Therapy (ECT)

There are no clinical studies of the combined use of ECT and nefazodone.

Carcinogenesis, Mutagenesis, Impairment of Fertility

Carcinogenesis

There is no evidence of carcinogenicity with nefazodone. The dietary administration of nefazodone to rats and mice for 2 years at daily doses of up to 200 mg/kg and 800 mg/kg, respectively, which are approximately 3 and 6 times, respectively, the maximum human daily dose on a mg/m^2 basis, produced no increase in tumors.

Mutagenesis

Nefazodone has been shown to have no genotoxic effects based on the following assays: bacterial mutation assays, a DNA repair assay in cultured rat hepatocytes, a mammalian mutation assay in Chinese hamster ovary cells, an in vivo cytogenetics assay in rat bone marrow cells, and a rat dominant lethal study.

Impairment of Fertility

A fertility study in rats showed a slight decrease in fertility at 200 mg/kg/day (approximately three times the maximum human daily dose on a mg/m^2 basis) but not at 100 mg/kg/day (approximately 1.5 times the maximum human daily dose on a mg/m^2 basis).

Pregnancy

Teratogenic Effects

Pregnancy category C

Reproduction studies have been performed in pregnant rabbits and rats at daily doses up to 200 and 300 mg/kg, respectively (approximately 6 and 5 times, respectively, the maximum human daily dose on a mg/m^2 basis). No malformations were observed in the offspring as a result of nefazodone treatment. However, increased early pup mortality was seen in rats at a dose approximately five times the maximum human dose, and decreased pup weights were seen at this and lower doses, when dosing began during pregnancy and continued until weaning. The cause of these deaths is not known. The no-effect dose for rat pup mortality was 1.3 times the human dose on a mg/m^2 basis. There are no adequate and well-controlled studies in pregnant women. Nefazodone should be used during pregnancy only if the potential benefit justifies the potential risk to the fetus.

Labor and Delivery

The effect of nefazodone on labor and delivery in humans is unknown.

Nursing Mothers

It is not known whether nefazodone or its metabolites are excreted in human milk. Because many drugs are excreted in human milk, caution should be exercised when nefazodone is administered to a nursing woman.

Pediatric Use

Safety and effectiveness in the pediatric population have not been established (see BOXED WARNING and WARNINGS, Clinical Worsening and Suicide Risk). Two placebo-controlled trials in 286 pediatric patients with MDD have been conducted with nefazodone, and the data were not sufficient to support a claim for use in pediatric patients. Anyone considering the use of nefazodone hydrochloride tablets in a child or adolescent must balance the potential risks with the clinical need.

Geriatric Use

Of the approximately 7000 patients in clinical studies who received nefazodone for the treatment of depression, 18% were 65 years and older, while 5% were 75 years and older. Based on monitoring of adverse events, vital signs, electrocardiograms, and results of laboratory tests, no overall differences in safety between elderly and younger patients were observed in clinical studies. Efficacy in the elderly has not been demonstrated in placebo-controlled trials. Other reported clinical experience has not identified differences in responses between elderly and younger patients, but greater sensitivity of some older individuals cannot be ruled out.

Due to the increased systemic exposure to nefazodone seen in single-dose studies in elderly patients (see CLINICAL PHARMACOLOGY, Pharmacokinetics), treatment should be initiated at half the usual dose, but titration upward should take place over the same range as in younger patients (see DOSAGE AND ADMINISTRATION). The usual precautions should be observed in elderly patients who have concomitant medical illnesses or who are receiving concomitant drugs.

ADVERSE REACTIONS

Associated with Discontinuation of Treatment

Approximately 16% of the 3496 patients who received nefazodone in worldwide premarketing clinical trials discontinued treatment due to an adverse experience. The more common (≥ 1%) events in clinical trials associated with discontinuation and considered to be drug related (i.e., those events associated with dropout at a rate approximately twice or greater for nefazodone compared to placebo) included: nausea (3.5%), dizziness (1.9%), insomnia (1.5%), asthenia (1.3%), and agitation (1.2%).

Incidence in Controlled Trials

Commonly Observed Adverse Events in Controlled Clinical Trials

The most commonly observed adverse events associated with the use of nefazodone (incidence of 5% or greater) and not seen at an equivalent incidence among placebo-treated patients (i.e., significantly higher incidence for nefazodone compared to placebo, p ≤ 0.05), derived from the table below, were: somnolence, dry mouth, nausea, dizziness, constipation, asthenia, lightheadedness, blurred vision, confusion, and abnormal vision.

Adverse Events Occurring at an Incidence of 1% or More Among Nefazodone-Treated Patients

The table that follows enumerates adverse events that occurred at an incidence of 1% or more, and were more frequent than in the placebo group, among nefazodone-treated patients who participated in short-term (6 to 8 week) placebo-controlled trials in which patients were dosed with nefazodone to ranges of 300 to 600 mg/day. This table shows the percentage of patients in each group who had at least one episode of an event at some time during their treatment. Reported adverse events were classified using standard COSTART-based Dictionary terminology.

The prescriber should be aware that these figures cannot be used to predict the incidence of side effects in the course of usual medical practice where patient characteristics and other factors differ from those which prevailed in the clinical trials. Similarly, the cited frequencies cannot be compared with figures obtained from other clinical investigations involving different treatments, uses, and investigators. The cited figures, however, do provide the prescribing physician with some basis for estimating the relative contribution of drug and nondrug factors to the side-effect incidence rate in the population studied.

Treatment-Emergent Adverse Experience Incidence in 6 to 8 Week Placebo-Controlled Clinical Trialsa, Nefazodone 300 to 600 mg/day Dose Range
 |  | Percent of Patients
Body System | Preferred Term | Nefazodone (n = 393) | Placebo (n = 394)
Body as a Whole | Headache | 36 | 33
 | Asthenia | 11 | 5
 | Infection | 8 | 6
 | Flu syndrome | 3 | 2
 | Chills | 2 | 1
 | Fever | 2 | 1
 | Neck rigidity | 1 | 0
Cardiovascular | Postural hypotension | 4 | 1
 | Hypotension | 2 | 1
Dermatological | Pruritus | 2 | 1
 | Rash | 2 | 1
Gastrointestinal | Dry mouth | 25 | 13
 | Nausea | 22 | 12
 | Constipation | 14 | 8
 | Dyspepsia | 9 | 7
 | Diarrhea | 8 | 7
 | Increased appetite | 5 | 3
 | Nausea & vomiting | 2 | 1
Metabolic | Peripheral edema | 3 | 2
 | Thirst | 1 | < 1
Musculoskeletal | Arthralgia | 1 | < 1
Nervous | Somnolence | 25 | 14
 | Dizziness | 17 | 5
 | Insomnia | 11 | 9
 | Lightheadedness | 10 | 3
 | Confusion | 7 | 2
 | Memory impairment | 4 | 2
 | Paresthesia | 4 | 2
 | Vasodilatationb | 4 | 2
 | Abnormal dreams | 3 | 2
 | Concentration decreased | 3 | 1
 | Ataxia | 2 | 0
 | Incoordination | 2 | 1
 | Psychomotor retardation | 2 | 1
 | Tremor | 2 | 1
 | Hypertonia | 1 | 0
 | Libido decreased | 1 | < 1
Respiratory | Pharyngitis | 6 | 5
 | Cough increased | 3 | 1
Special Senses | Blurred vision | 9 | 3
 | Abnormal visionc | 7 | 1
 | Tinnitus | 2 | 1
 | Taste perversion | 2 | 1
 | Visual field defect | 2 | 0
Urogenital | Urinary frequency | 2 | 1
 | Urinary tract infection | 2 | 1
 | Urinary retention | 2 | 1
 | Vaginitisd | 2 | 1
 | Breast paind | 1 | < 1

1. Events reported by at least 1% of patients treated with nefazodone and more frequent than the placebo group are included; incidence is rounded to the nearest 1% (< 1% indicates an incidence less than 0.5%). Events for which the nefazodone incidence was equal to or less than placebo are not listed in the table, but included the following: abdominal pain, pain, back pain, accidental injury, chest pain, neck pain, palpitation, migraine, sweating, flatulence, vomiting, anorexia, tooth disorder, weight gain, edema, myalgia, cramp, agitation, anxiety, depression, hypesthesia, CNS stimulation, dysphoria, emotional lability, sinusitis, rhinitis, dysmenorrhead, dysuria.
2. Vasodilatation – flushing, feeling warm.
3. Abnormal vision – scotoma, visual trails.
4. Incidence adjusted for gender.

Dose Dependency of Adverse Events

The table that follows enumerates adverse events that were more frequent in the nefazodone dose range of 300 to 600 mg/day than in the nefazodone dose range of up to 300 mg/day. This table shows only those adverse events for which there was a statistically significant difference (p ≤ 0.05) in incidence between the nefazodone dose ranges as well as a difference between the high dose range and placebo.

Dose Dependency of Adverse Events in Placebo-Controlled Trialsa
 |  | Percent of Patients
Body System | Preferred Term | Nefazodone; 300 to 600 mg/day; (n = 209) | Nefazodone; ≤ 300 mg/day; (n = 211) | Placebo; (n = 212)
Gastrointestinal | Nausea | 23 | 14 | 12
 | Constipation | 17 | 10 | 9
Nervous | Somnolence | 28 | 16 | 13
 | Dizziness | 22 | 11 | 4
 | Confusion | 8 | 2 | 1
Special Senses | Abnormal Vision | 10 | 0 | 2
 | Blurred Vision | 9 | 3 | 2
 | Tinnitus | 3 | 0 | 1

a. Events for which there was a statistically significant difference (p ≤ 0.05) between the nefazodone dose groups.

Visual Disturbances

In controlled clinical trials, blurred vision occurred in 9% of nefazodone-treated patients compared to 3% of placebo-treated patients. In these same trials abnormal vision, including scotomata and visual trails, occurred in 7% of nefazodone-treated patients compared to 1% of placebo-treated (see Treatment-Emergent Adverse Experience table, above). Dose-dependency was observed for these events in these trials, with none of the scotomata and visual trails at doses below 300 mg/day. However, scotomata and visual trails observed at doses below 300 mg/day have been reported in postmarketing experience with nefazodone (see PRECAUTIONS, Information for Patients).

Vital Sign Changes

(See PRECAUTIONS, Postural Hypotension.)

Weight Changes

In a pooled analysis of placebo-controlled premarketing studies, there were no differences between nefazodone and placebo groups in the proportions of patients meeting criteria for potentially important increases or decreases in body weight (a change of ≥ 7%).

Laboratory Changes

Of the serum chemistry, serum hematology, and urinalysis parameters monitored during placebo-controlled premarketing studies with nefazodone, a pooled analysis revealed a statistical trend between nefazodone and placebo for hematocrit, i.e., 2.8% of nefazodone patients met criteria for a potentially important decrease in hematocrit (≤ 37% male or ≤ 32% female) compared to 1.5% of placebo patients (0.05 < p ≤ 0.10). Decreases in hematocrit, presumably dilutional, have been reported with many other drugs that block alpha1-adrenergic receptors. There was no apparent clinical significance of the observed changes in the few patients meeting these criteria.

ECG Changes

Of the ECG parameters monitored during placebo-controlled premarketing studies with nefazodone, a pooled analysis revealed a statistically significant difference between nefazodone and placebo for sinus bradycardia, i.e., 1.5% of nefazodone patients met criteria for a potentially important decrease in heart rate (≤ 50 bpm and a decrease of ≥ 15 bpm) compared to 0.4% of placebo patients (p < 0.05). There was no obvious clinical significance of the observed changes in the few patients meeting these criteria.

Other Events Observed During the Premarketing Evaluation of Nefazodone

During its premarketing assessment, multiple doses of nefazodone were administered to 3496 patients in clinical studies, including more than 250 patients treated for at least one year. The conditions and duration of exposure to nefazodone varied greatly, and included (in overlapping categories) open and double-blind studies, uncontrolled and controlled studies, inpatient and outpatient studies, fixed-dose and titration studies. Untoward events associated with this exposure were recorded by clinical investigators using terminology of their own choosing. Consequently, it is not possible to provide a meaningful estimate of the proportion of individuals experiencing adverse events without first grouping similar types of untoward events into a smaller number of standardized event categories.

In the tabulations that follow, reported adverse events were classified using standard COSTART-based Dictionary terminology. The frequencies presented, therefore, represent the proportion of the 3496 patients exposed to multiple doses of nefazodone who experienced an event of the type cited on at least one occasion while receiving nefazodone. All reported events are included except those already listed in the Treatment-Emergent Adverse Experience Incidence table, those events listed in other safety-related sections of this insert, those adverse experiences subsumed under COSTART terms that are either overly general or excessively specific so as to be uninformative, those events for which a drug cause was very remote, and those events which were not serious and occurred in fewer than two patients.

It is important to emphasize that, although the events reported occurred during treatment with nefazodone, they were not necessarily caused by it.

Events are further categorized by body system and listed in order of decreasing frequency according to the following definitions: frequent adverse events are those occurring on one or more occasions in at least 1/100 patients (only those not already listed in the tabulated results from placebo-controlled trials appear in this listing); infrequent adverse events are those occurring in 1/100 to 1/1000 patients; rare events are those occurring in fewer than 1/1000 patients.

Body as a whole – Infrequent: allergic reaction, malaise, photosensitivity reaction, face edema, hangover effect, abdomen enlarged, hernia, pelvic pain, and halitosis. Rare: cellulitis.

Cardiovascular system – Infrequent: tachycardia, hypertension, syncope, ventricular extrasystoles, and angina pectoris. Rare: AV block, congestive heart failure, hemorrhage, pallor, and varicose vein.

Dermatological system – Infrequent: dry skin, acne, alopecia, urticaria, maculopapular rash, vesiculobullous rash, and eczema.

Gastrointestinal system – Frequent: gastroenteritis. Infrequent: eructation, periodontal abscess, abnormal liver function tests, gingivitis, colitis, gastritis, mouth ulceration, stomatitis, esophagitis, peptic ulcer, and rectal hemorrhage. Rare: glossitis, hepatitis, dysphagia, gastrointestinal hemorrhage, oral moniliasis, and ulcerative colitis.

Hemic and lymphatic system – Infrequent: ecchymosis, anemia, leukopenia, and lymphadenopathy.

Metabolic and nutritional system – Infrequent: weight loss, gout, dehydration, lactic dehydrogenase increased, SGOT increased, and SGPT increased. Rare: hypercholesteremia and hypoglycemia.

Musculoskeletal system – Infrequent: arthritis, tenosynovitis, muscle stiffness, and bursitis. Rare: tendinous contracture.

Nervous system – Infrequent: vertigo, twitching, depersonalization, hallucinations, suicide attempt, apathy, euphoria, hostility, suicidal thoughts, abnormal gait, thinking abnormal, attention decreased, derealization, neuralgia, paranoid reaction, dysarthria, increased libido, suicide, and myoclonus. Rare: hyperkinesia, increased salivation, cerebrovascular accident, hyperesthesia, hypotonia, ptosis, and neuroleptic malignant syndrome.

Respiratory system – Frequent: dyspnea and bronchitis. Infrequent: asthma, pneumonia, laryngitis, voice alteration, epistaxis, hiccup. Rare: hyperventilation and yawn.

Special senses – Frequent: eye pain. Infrequent: dry eye, ear pain, abnormality of accommodation, diplopia, conjunctivitis, mydriasis, keratoconjunctivitis, hyperacusis, and photophobia. Rare: deafness, angle-closure glaucoma, night blindness, and taste loss.

Urogenital system – Frequent: impotencea. Infrequent: cystitis, urinary urgency, metrorrhagiaa, amenorrheaa, polyuria, vaginal hemorrhagea, breast enlargementa, menorrhagiaa, urinary incontinence, abnormal ejaculationa, hematuria, nocturia, and kidney calculus. Rare: uterine fibroids enlargeda, uterine hemorrhagea, anorgasmia, and oliguria.

a Adjusted for gender.

Postintroduction Clinical Experience

Postmarketing experience with nefazodone has shown an adverse experience profile similar to that seen during the premarketing evaluation of nefazodone. Voluntary reports of adverse events temporally associated with nefazodone have been received since market introduction that are not listed above and for which a causal relationship has not been established. These include:

Anaphylactic reactions; angioedema; convulsions (including grand mal seizures); galactorrhea; gynecomastia (male); hyponatremia; liver necrosis and liver failure, in some cases leading to liver transplantation and/or death (see WARNINGS); priapism (see PRECAUTIONS); prolactin increased; rhabdomyolysis involving patients receiving the combination of nefazodone and lovastatin or simvastatin (see PRECAUTIONS); serotonin syndrome; and Stevens-Johnson syndrome; and thrombocytopenia.

To report SUSPECTED ADVERSE EVENTS, contact Teva at 1-888-838-2872 or FDA at 1-800-FDA-1088 or http://www.fda.gov/medwatch for voluntary reporting of adverse reactions.

DRUG ABUSE AND DEPENDENCE

Controlled Substance Class

Nefazodone is not a controlled substance.

Physical and Psychological Dependence

In animal studies, nefazodone did not act as a reinforcer for intravenous self-administration in monkeys trained to self-administer cocaine, suggesting no abuse liability. In a controlled study of abuse liability in human subjects, nefazodone showed no potential for abuse.

Nefazodone has not been systematically studied in humans for its potential for tolerance, physical dependence, or withdrawal. While the premarketing clinical experience with nefazodone did not reveal any tendency for a withdrawal syndrome or any drug-seeking behavior, it is not possible to predict on the basis of this limited experience the extent to which a CNS-active drug will be misused, diverted, and/or abused once marketed. Consequently, physicians should carefully evaluate patients for a history of drug abuse and follow such patients closely, observing them for signs of misuse or abuse of nefazodone (e.g., development of tolerance, dose escalation, drug-seeking behavior).

OVERDOSAGE

Human Experience

In premarketing clinical studies, there were seven reports of nefazodone overdose alone or in combination with other pharmacological agents. The amount of nefazodone ingested ranged from 1000 mg to 11,200 mg. Commonly reported symptoms from overdose of nefazodone included nausea, vomiting, and somnolence. One nonstudy participant took 2000 to 3000 mg of nefazodone with methocarbamol and alcohol; this person reportedly experienced a convulsion (type not documented). None of these patients died.

In postmarketing experience, overdose with nefazodone alone and in combination with alcohol and/or other substances has been reported. Commonly reported symptoms were similar to those reported from overdose in premarketing experience. While there have been rare reports of fatalities in patients taking overdoses of nefazodone, predominantly in combination with alcohol and/or other substances, no causal relationship to nefazodone has been established.

Overdosage Management

Treatment should consist of those general measures employed in the management of overdosage with any antidepressant.

Ensure an adequate airway, oxygenation, and ventilation. Monitor cardiac rhythm and vital signs. General supportive and symptomatic measures are also recommended. Induction of emesis is not recommended. Gastric lavage with a large-bore orogastric tube with appropriate airway protection, if needed, may be indicated if performed soon after ingestion, or in symptomatic patients.

Activated charcoal should be administered. Due to the wide distribution of nefazodone in body tissues, forced diuresis, dialysis, hemoperfusion, and exchange transfusion are unlikely to be of benefit. No specific antidotes for nefazodone are known.

In managing overdosage, consider the possibility of multiple drug involvement. The physician should consider contacting a poison control center for additional information on the treatment of any overdose. Telephone numbers for certified poison control centers are listed in the Physicians’ Desk Reference (PDR).

DOSAGE AND ADMINISTRATION

When deciding among the alternative treatments available for depression, the prescriber should consider the risk of hepatic failure associated with nefazodone hydrochloride treatment (see WARNINGS).

Initial Treatment

The recommended starting dose for nefazodone hydrochloride tablets USP is 200 mg/day, administered in two divided doses (BID). In the controlled clinical trials establishing the antidepressant efficacy of nefazodone, the effective dose range was generally 300 to 600 mg/day. Consequently, most patients, depending on tolerability and the need for further clinical effect, should have their dose increased. Dose increases should occur in increments of 100 mg/day to 200 mg/day, again on a BID schedule, at intervals of no less than 1 week. As with all antidepressants, several weeks on treatment may be required to obtain a full antidepressant response.

Dosage for Elderly or Debilitated Patients

The recommended initial dose for elderly or debilitated patients is 100 mg/day, administered in two divided doses (BID). These patients often have reduced nefazodone clearance and/or increased sensitivity to the side effects of CNS-active drugs. It may also be appropriate to modify the rate of subsequent dose titration. As steady-state plasma levels do not change with age, the final target dose based on a careful assessment of the patient’s clinical response may be similar in healthy younger and older patients.

Maintenance/Continuation/Extended Treatment

There is no body of evidence available from controlled trials to indicate how long the depressed patient should be treated with nefazodone. It is generally agreed, however, that pharmacological treatment for acute episodes of depression should continue for up to 6 months or longer. Whether the dose of antidepressant needed to induce remission is identical to the dose needed to maintain euthymia is unknown. Systematic evaluation of the efficacy of nefazodone has shown that efficacy is maintained for periods of up to 36 weeks following 16 weeks of open-label acute treatment (treated for 52 weeks total) at dosages that averaged 438 mg/day. For most patients, their maintenance dose was that associated with response during acute treatment (see CLINICAL PHARMACOLOGY). The safety of nefazodone in long-term use is supported by data from both double-blind and open-label trials involving more than 250 patients treated for at least one year.

Switching Patients to or From a Monoamine Oxidase Inhibitor

At least 14 days should elapse between discontinuation of an MAOI and initiation of therapy with nefazodone. In addition, at least 7 days should be allowed after stopping nefazodone before starting an MAOI.

HOW SUPPLIED

Nefazodone hydrochloride tablets USP, 150 mg, are peach (mottled), capsule-shaped tablets, debossed “7113” on one side and scored on the other side with a debossed “93” on one side of the score.

- NDC 63629-7046-1: 30 Tablets in a BOTTLE
- NDC 63629-7046-2: 120 Tablets in a BOTTLE
- NDC 63629-7046-3: 28 Tablets in a BOTTLE
- NDC 63629-7046-4: 60 Tablets in a BOTTLE

Store at 20° to 25°C (68° to 77°F) [see USP Controlled Room Temperature].

Dispense in a tight, light-resistant container as defined in the USP, with a child-resistant closure (as required).

Repackaged/Relabeled by:
Bryant Ranch Prepack, Inc.
Burbank, CA 91504

PATIENT INFORMATION

Nefazodone Hydrochloride (ne faz' oh done hye" droe klorʹ ide) Tablets

Rx only

Read this information completely before using nefazodone. Read the information each time you get more medicine. There may be new information. This leaflet provides a summary about nefazodone and does not include everything there is to know about your medicine. This information is not meant to take the place of talking with your doctor.

What is the most important information that I should know about nefazodone?

Rarely, people who take nefazodone can develop serious liver problems. If you get any of the following symptoms while taking nefazodone, call your doctor right away because you may be developing a liver problem:

- Yellowing of the skin or whites of eyes (jaundice)
- Unusually dark urine
- Loss of appetite that lasts several days or longer
- Nausea
- Abdominal (lower stomach) pain

People who currently have liver problems should not take nefazodone.

What is nefazodone?

Nefazodone is a medicine used to treat depression. Nefazodone is thought to treat depression by correcting an imbalance in the amounts of certain natural chemicals, such as serotonin and norepinephrine, which are in your brain.

Who should not take nefazodone?

Do not take nefazodone if you

- are allergic to nefazodone or the related medicine Desyrel® (trazodone).
- are taking Seldane® (terfenadine), an antihistamine; Hismanal® (astemizole), an antihistamine; Propulsid® (cisapride), used for heartburn; Halcion® (triazolam), used for insomnia; Orap® (pimozide), used to treat Tourette’s syndrome; or Tegretol® (carbamazepine), used to control seizures.
- currently have liver problems.
- are taking or have taken within the last 14 days one of the medicines for depression known as monoamine oxidase inhibitors (MAOIs), such as Nardil® or Parnate®.

Be sure to tell your doctor if you

- have ever had liver problems;
- are taking any other medicine, vitamin supplement, or herbal remedy, including those sold without a prescription (over-the-counter);
- have heart problems or have had a heart attack or stroke;
- have had manic episodes (extreme agitation or excitability);
- have ever attempted suicide;
- have had convulsions (seizures);
- are pregnant or breast-feeding.

How should I take nefazodone?

- Take nefazodone at the same time every day exactly as prescribed by your doctor. You may take nefazodone with or without food.
- It may take a while for you to feel that nefazodone is working. You may not feel the full effect for several weeks. Once you feel better, it is important to keep taking nefazodone as directed by your doctor.
- If you miss a dose of nefazodone, skip that dose and continue with your regular schedule. Never take 2 doses at the same time.
- If you think that you have taken more nefazodone than prescribed, contact your doctor, local poison control center, or emergency room right away.

What should I avoid while taking nefazodone?

- Do not drive or operate possibly dangerous machinery (such as an automobile, power mower, or power tool) or participate in any hazardous activity that requires full mental alertness until you know how nefazodone affects you.
- Before taking nefazodone, tell your doctor about any medicines you are taking, including vitamin supplements, herbal remedies, and any non-prescription (over-the-counter) medicines. Some of these medicines may affect how nefazodone works and should not be used in combination without talking to your doctor.
- Do not drink alcoholic beverages while taking nefazodone.
- Tell your doctor if you are pregnant, planning to become pregnant, or become pregnant while taking nefazodone. It is not known whether nefazodone can harm your unborn baby.
- Talk with your doctor before taking nefazodone if you are breast-feeding. It is not known whether nefazodone can pass through your breast milk to the baby.

What are the possible side effects of nefazodone?

The most common side effects of nefazodone are sleepiness, dry mouth, nausea, dizziness, constipation, weakness, lightheadedness, problems with vision, and confusion.

Call your doctor right away if you have any of the following side effects:

- Yellowing of the skin or whites of eyes (jaundice)
- Unusually dark urine
- Loss of appetite that lasts several days or longer
- Severe nausea
- Abdominal (lower stomach) pain
- Rash or hives
- Seizure (convulsion)
- Fainting
- Erection that lasts too long

Tell your doctor right away about any side effects that you have or discomfort that you experience. Do not change your dose or stop taking nefazodone without talking with your doctor first.

Medicines are sometimes prescribed for conditions that are not mentioned in patient information leaflets. Your doctor has prescribed nefazodone for you and you alone. Do not give nefazodone to other people even if they have the same condition. It may harm them.

This leaflet provides a summary of the most important information about nefazodone. If you would like more information, talk with your doctor or pharmacist. You can ask for information about nefazodone that is written for healthcare professionals.

Brands listed are the trademarks of their registered owners.

Manufactured In Israel By:
Teva Pharmaceutical Ind. Ltd.
Kfar Saba, 4410202, Israel

Manufactured For:
Teva Pharmaceuticals
Parsippany, NJ 07054

Rev. C 10/2021

This Patient Information Leaflet has been approved by the U.S. Food and Drug Administration.

MEDICATION GUIDE

Dispense with Medication Guide available at: www.tevausa.com/medguides

Antidepressant Medicines, Depression and other Serious Mental Illnesses, and Suicidal Thoughts or Actions

Rx only

Read the Medication Guide that comes with your or your family member’s antidepressant medicine. This Medication Guide is only about the risk of suicidal thoughts and actions with antidepressant medicines. Talk to your, or your family member’s, healthcare provider about:

- all risks and benefits of treatment with antidepressant medicines
- all treatment choices for depression or other serious mental illness

What is the most important information I should know about antidepressant medicines, depression and other serious mental illnesses, and suicidal thoughts or actions?

1. Antidepressant medicines may increase suicidal thoughts or actions in some children, teenagers, and young adults within the first few months of treatment.

2. Depression and other serious mental illnesses are the most important causes of suicidal thoughts and actions. Some people may have a particularly high risk of having suicidal thoughts or actions. These include people who have (or have a family history of) bipolar illness (also called manic-depressive illness) or suicidal thoughts or actions.

3. How can I watch for and try to prevent suicidal thoughts and actions in myself or a family member?

- Pay close attention to any changes, especially sudden changes, in mood, behaviors, thoughts, or feelings. This is very important when an antidepressant medicine is started or when the dose is changed.
- Call the healthcare provider right away to report new or sudden changes in mood, behavior, thoughts, or feelings.
- Keep all follow-up visits with the healthcare provider as scheduled. Call the healthcare provider between visits as needed, especially if you have concerns about symptoms.

Call a healthcare provider right away if you or your family member has any of the following symptoms, especially if they are new, worse, or worry you:

- thoughts about suicide or dying
- attempts to commit suicide
- new or worse depression
- new or worse anxiety
- feeling very agitated or restless
- panic attacks
- trouble sleeping (insomnia)
- new or worse irritability
- acting aggressive, being angry, or violent
- acting on dangerous impulses
- an extreme increase in activity and talking (mania)
- other unusual changes in behavior or mood
- Visual problems: eye pain, changes in vision, swelling or redness in or around the eye

What else do I need to know about antidepressant medicines?

- Never stop an antidepressant medicine without first talking to a healthcare provider. Stopping an antidepressant medicine suddenly can cause other symptoms.
- Visual problems: Only some people are at risk for these problems. You may want to undergo an eye examination to see if you are at risk and receive preventative treatment if you are.
- Antidepressants are medicines used to treat depression and other illnesses. It is important to discuss all the risks of treating depression and also the risks of not treating it. Patients and their families or other caregivers should discuss all treatment choices with the healthcare provider, not just the use of antidepressants.
- Antidepressant medicines have other side effects. Talk to the healthcare provider about the side effects of the medicine prescribed for you or your family member.
- Antidepressant medicines can interact with other medicines. Know all of the medicines that you or your family member takes. Keep a list of all medicines to show the healthcare provider. Do not start new medicines without first checking with your healthcare provider.
- Not all antidepressant medicines prescribed for children are FDA approved for use in children. Talk to your child’s healthcare provider for more information.

Call your doctor for medical advice about side effects. You may report side effects to FDA at 1-800-FDA-1088.

This Medication Guide has been approved by the U.S. Food and Drug Administration for all antidepressants.

Manufactured In Israel By:
Teva Pharmaceutical Ind. Ltd.
Kfar Saba, 4410202, Israel

Manufactured For:
Teva Pharmaceuticals
Parsippany, NJ 07054

Rev. H 10/2021

PACKAGE LABEL

Nefazodone Hydrochloride 150mg Tablets